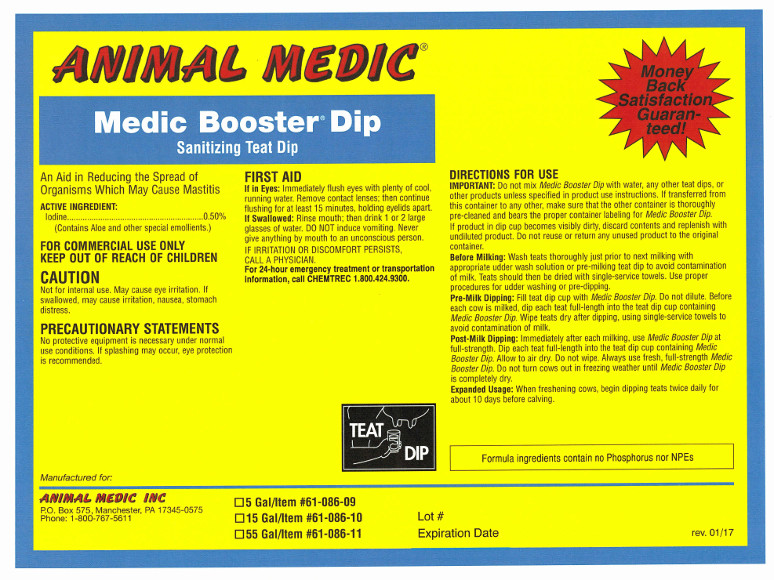 DRUG LABEL: Medic Booster Dip
NDC: 12994-001 | Form: LIQUID
Manufacturer: Animal Medic Incorporated
Category: animal | Type: OTC ANIMAL DRUG LABEL
Date: 20170130

ACTIVE INGREDIENTS: IODINE 5000 mg/1 L

Medic Booster Dip

USER SAFETY WARNINGS

Sanitizing Teat Dip

An aid in reducing the spread of organisms which may cause mastitis.

ACTIVE INGREDIENT:

Iodine .................................................................... 0.50%

(Contains Aloe and other special emollients.)

FOR COMMERCIAL USE ONLY

KEEP OUT OF REACH OF CHILDREN

CAUTION

Not for internal use. May cause eye irritation. If swallowed, may cause irritation, nausea, stomach distress.

PRECAUTIONARY STATEMENTS

No protective equipment is necessary under normal use conditions. If splashing may occur, eye protection is recommended.

FIRST AID

If in Eyes: Immediately flush eyes with plenty of cool, running water. Remove contact lenses; then continue flushing for at least 15 minutes, holding eyelids apart.

If Swallowed: Rinse mouth; then drink 1 or 2 glasses of water. DO NOT induce vomiting. Never give anything by mouth to an unconscious person. IF IRRITATION OR DISCOMFORT PERSISTS, CALL A PHYSICIAN.

For 24-hour emergency treatment or transportation information, call CHEMTREC 1.800.424.9300.

DOSAGE AND ADMINISTRATION

DIRECTIONS FOR USE

IMPORTANT: Do not mix Medic Booster Dip with water, any other teat dips, or other products unless specified in product use instructions. If transferred from this container to any other, make sure that the other container is clean and bears the proper container label for Medic Booster Dip. If product in dip cup becomes visibly dirty, discard contents and replenish with undiluted product.
Do not reuse or return any unused product to the original container.

Before Milking: Wash teats thoroughly just prior to next milking with appropriate udder wash solution or pre-milking teat dip to avoid contamination of milk. Teats should be dried with single-service towels. Use proper procedures for udder washing or pre-dipping.

Pre-Milk Dipping: Fill teat cup with Medic Booster Dip. Do not dilute. Before each cow is milked, dip each teat full-length into the teat cup containing Medic Booster Dip. Wipe teats dry after dipping using single-service towels to avoid contamination of milk.

Post-Milk Dipping: Immediately after each milking, use Medic Booster Dip at full strength. Dip each teat full-length into the teat cup containing Medic Booster Dip. Allow to air dry. Do not wipe. Always use fresh, full-strength Medic Booster Dip. Do not turn cows out in freezing weather until Medic Booster Dip is completely dry.

Expanded Usage: When freshening cows, begin dipping teats twice daily for about ten days before calving.

Formula ingredients contain no Phosphorus nor NPEs